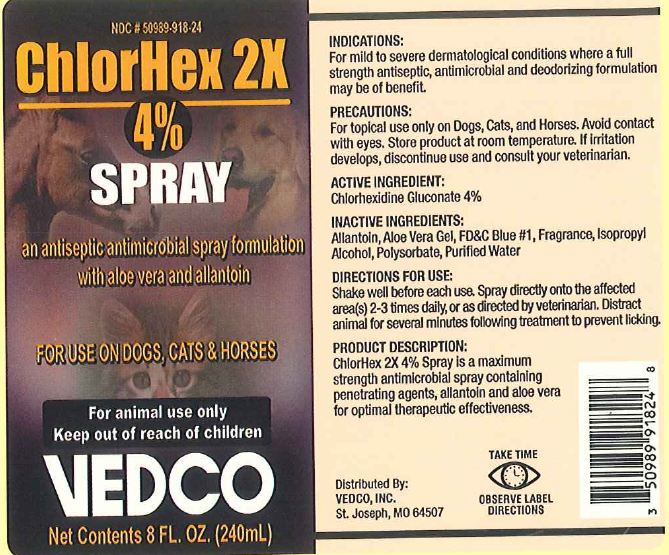 DRUG LABEL: ChlorHex 2X
NDC: 50989-918 | Form: SPRAY
Manufacturer: Vedco, Inc
Category: animal | Type: OTC ANIMAL DRUG LABEL
Date: 20120615

ACTIVE INGREDIENTS: CHLORHEXIDINE GLUCONATE 40.000 g/1.0 L

ChlorHex 2X

Indications:

For Mild to severe dermatological conditions where a full strength antiseptic, antimicrobial and deodorizing formulation may be of benefit.

Precautions:

For topical use only on Dogs, Cats and Horses. Avoid contact with eyes. If irritation develops, discontinue use and consult your veterinarian.

Storage

Store product at room temperature.

Active Ingredient:

Chlorhexidine Gluconate 4%

Inactive Ingredients:

Allantoin, Aloe Vera Gel, FD&C Blue #1, Fragrance, Isopropyl Alcohol, Polysorbate, Purified Water

Directions for Use:

Shake well before each use. Spray directly onto the affected area(s) 2-3 times daily, or as directed by veterinarian. Distract animal for several minutes following treatment to prevent licking.

Product Description

ChlorHex 2X 4% Spray is a maximum strength antimicrobial spray containing penetrating agents, allantoin and aloe vera for optimal thera peutic effectiveness.

Package Label

Label for 8oz product:

ChlorHex Spray

Distributed By

VEDCO, INC.

St. Joseph, MO 64507

Other Safety Information

TAKE TIME

OBSERVE LABEL DIRECTIONS